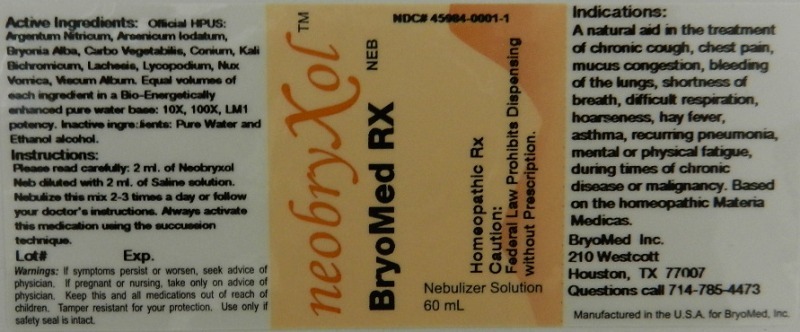 DRUG LABEL: neobryxol Neb
NDC: 45984-0001 | Form: LIQUID
Manufacturer: Bryomed Inc
Category: homeopathic | Type: HUMAN PRESCRIPTION DRUG LABEL
Date: 20120221

ACTIVE INGREDIENTS: SILVER NITRATE 10 [hp_X]/60 mL; ARSENIC TRIIODIDE 10 [hp_X]/60 mL; BRYONIA ALBA ROOT 10 [hp_X]/60 mL; ACTIVATED CHARCOAL 10 [hp_X]/60 mL; CONIUM MACULATUM FLOWERING TOP 10 [hp_X]/60 mL; POTASSIUM DICHROMATE 10 [hp_X]/60 mL; LACHESIS MUTA VENOM 10 [hp_X]/60 mL; LYCOPODIUM CLAVATUM SPORE 10 [hp_X]/60 mL; STRYCHNOS NUX-VOMICA SEED 10 [hp_X]/60 mL; VISCUM ALBUM WHOLE 10 [hp_X]/60 mL
INACTIVE INGREDIENTS: WATER; ALCOHOL

NeobryXol Neb

Active Ingredients

Official HPUS: Argentum nitricum, Arsenicum iodatum, Bryonia, Carbo vegetabiles, Conium Maculatum, Kali bichromicum, Lachesis mutus, Lycopodium, Nux vomica and Viscum album.

Reference image neb.jpg

Inactive Ingredients

Equal volumes of each ingredients in a Bio-Energetically Enhanced pure water base: 10X, 100X, LM1 potency. Inactive Ingredients: pure water and ethanol alcohol.

Reference image neb.jpg

Dosage and Administration

Instructions:

Please read carefully: 2 ml. of neobryxol Neb diluted with 2 ml. of saline solution. Nebulize this mix 2-3 times a day or follow your doctor's instructions. Always activate this medication using the succussion technique.

Reference image neb.jpg

Purpose

A natural aid in the treatment of:

- chronic cough
- chest pain
- mucus congestion
- bleeding of the lungs
- shortness of breath
- difficult respiration
- hoarseness
- hay fever
- asthma
- recurring pneumonia
- mental or physical fatigue during times of chronic disease or malignancy.

. Based on the homeopathic Materia Medicas.
Reference image neb.jpg

Warnings

If symptoms persist or worsen, seek advice of physician. If pregnant or nursing, take only on advice of physician. Keep this and all medications out of reach of children.

Tamper resistant for your protection. Use only if safety seal is intact.

Reference image neb.jpg

KEEP OUT OF REACH OF CHILDREN

Keep this and all medications out of reach of children.

Reference image neb.jpg

Indications and Usage

A natural aid in the treatment of chronic cough, chest pain, mucus congestion, bleeding of the lungs, shortness of breath, difficult respiration, hoarseness, hay fever, asthma, recurring pneumonia, mental or physical fatigue, during times of chronic disease or malignancy. Based on the homeopathic Materia Medicas.

Reference image neb.jpg

PACKAGE LABEL

BryoMed, Inc.

210 Westcott

Houston, TX 77007

Question call 714-785-4473